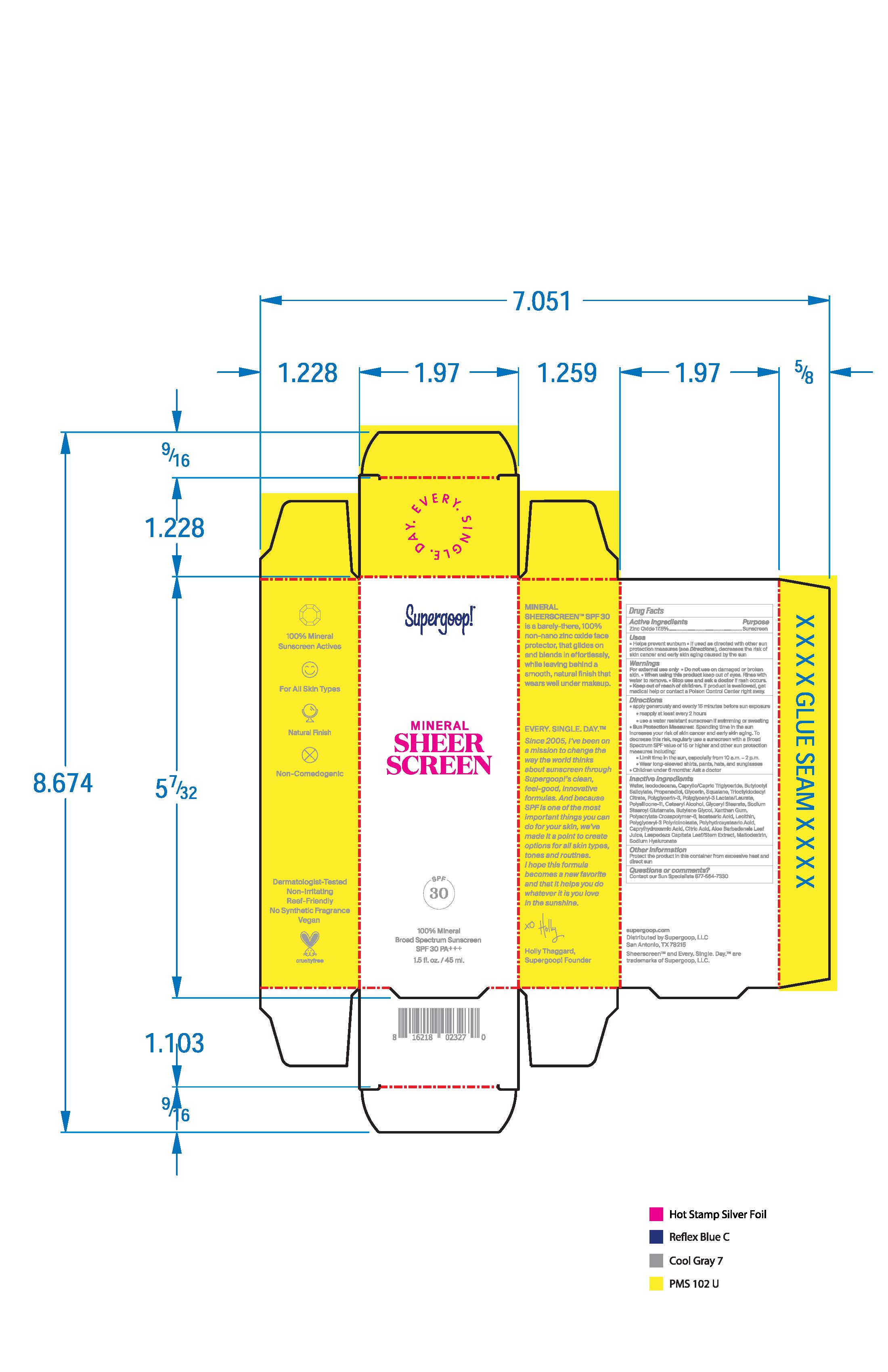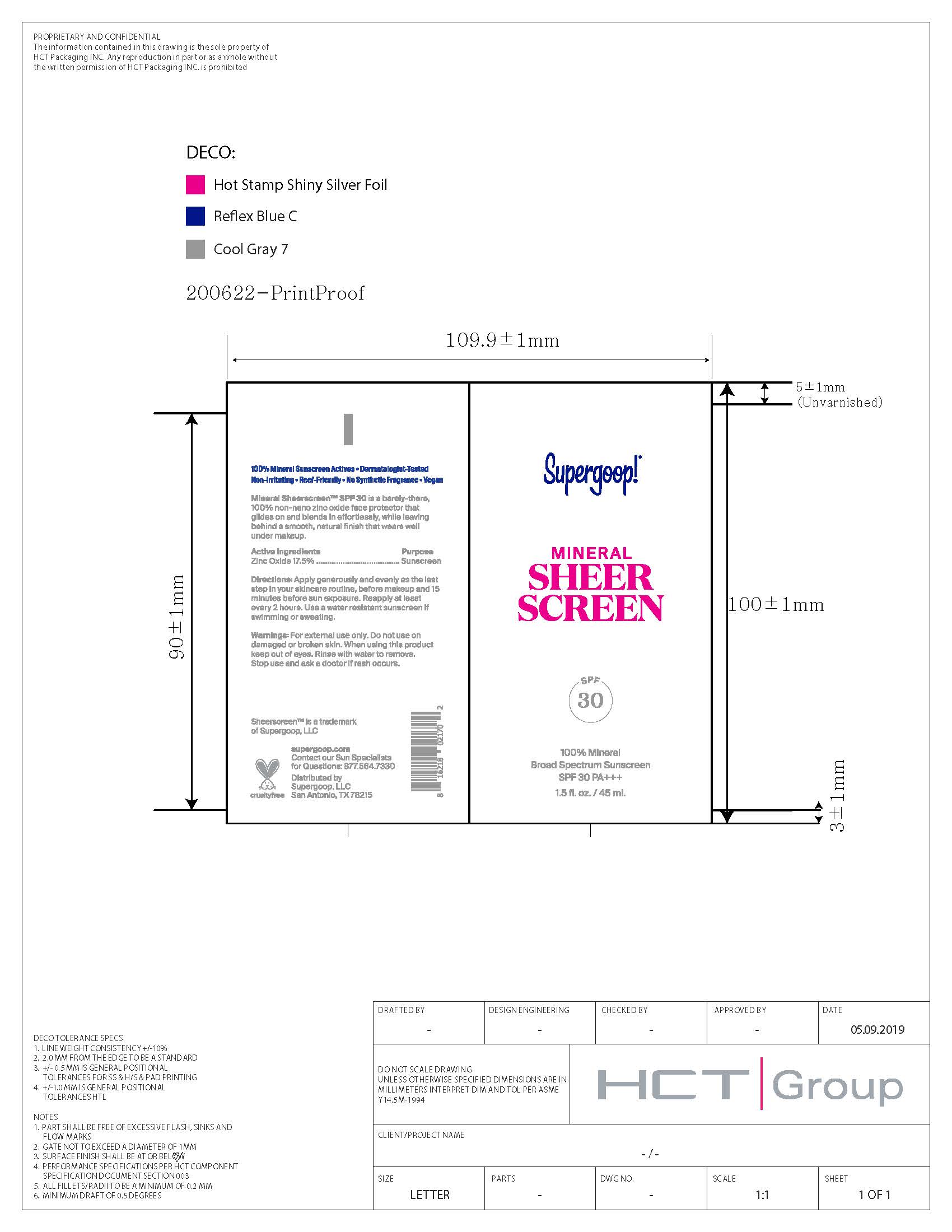 DRUG LABEL: Mineral Sheer Screen Broad Spectrum Sunscreen SPF 30
NDC: 75936-305 | Form: LOTION
Manufacturer: Supergoop LLC
Category: otc | Type: HUMAN OTC DRUG LABEL
Date: 20241216

ACTIVE INGREDIENTS: ZINC OXIDE 17.5 g/100 mL
INACTIVE INGREDIENTS: ISODODECANE; MEDIUM-CHAIN TRIGLYCERIDES; GLYCERIN; TRIOCTYLDODECYL CITRATE; GLYCERYL MONOSTEARATE; BUTYLENE GLYCOL; POLYGLYCERYL-3 PENTARICINOLEATE; POLYHYDROXYSTEARIC ACID (2300 MW); CAPRYLHYDROXAMIC ACID; AMMONIUM ACRYLOYLDIMETHYLTAURATE, DIMETHYLACRYLAMIDE, LAURYL METHACRYLATE AND LAURETH-4 METHACRYLATE COPOLYMER, TRIMETHYLOLPROPANE TRIACRYLATE CROSSLINKED (45000 MPA.S); SODIUM STEAROYL GLUTAMATE; POLYGLYCERIN-3; DIMETHICONE/VINYL DIMETHICONE CROSSPOLYMER (SOFT PARTICLE); ALOE VERA LEAF; HYALURONATE SODIUM; BUTYLOCTYL SALICYLATE; PROPANEDIOL; SQUALANE; ISOSTEARIC ACID; LECITHIN, SOYBEAN; CETOSTEARYL ALCOHOL; XANTHAN GUM; CITRIC ACID MONOHYDRATE; MALTODEXTRIN; WATER

Mineral Sheer Screen Broad Spectrum Sunscreen SPF 30

Active Ingredient Purpose

Zinc Oxide 17.5% Sunscreen

PURPOSE

Sunscreen

Helps prevent sunburn.

If used as directed with other sun protection measures (see Directions), decreases the risk of skin cancer and early skin againg caused by the sun.

Keep out of reach of children. If product is swallowed, get medical help or contact a Poison Control Center right away.

Stop use and ask a doctor if rash occurs.

WARNINGS

For external use only

Do not use on damaged or broken skin

When using this product kee out of eyes. Rinse with water to remove.

DOSAGE AND ADMINISTRATION

- apply generously and evenly 15 minutes before sun exposure
  - reapply at least every 2 hours
- use a water resistant sunscreen if swimming or sweating
- Sun Protection Measures: Spending time in the sun increases your risk of skin cancer and early skin aging. To decrease this risk, regularly use a sunscreen with a Broad Spectrum SPF value of 15 or higher and other sun protection measures including:
- Limit time in the sun, especially from 10 a.m. - 2 p.m.
- Wear long-sleeved shirts, pants, hats, and sunglassess
- Children under 6 months: Ask a doctor.

INACTIVE INGREDIENT

Water, Isododecane, Caprylic/Capric Triglyceride, Butyloctyl Salicylate, Propanedlol, Glycerin, Squalane, Trioctyldodecyl Citrate, Polyglycerln-3, Polyglyceryl-3 Lactate/Laurate, Polysilicone-11, Cetearyl Alcohol, Glyceryl Stearate, Sodium Stearoyl Glutamate, Butylene Glycol, Xanthan Gum, Polyacrylate Crosspolymer-6, lsostearic Acid, Lecithin, Polyglyceryl-3 Polyricinoleate, Polyhydroxystearic Acid, Caprylhydroxamic Acid, Citric Acid, Aloe Barbadensis Leaf Juice, Lespedeza Capitata Leaf/Stem Extract, Maltodextrin, Sodium Hyaluronate

STORAGE AND HANDLING

Protect the product In this container from excessive heat and direct sun.

PACKAGE LABEL

Mineral Sheer Screen

SPF 30

100% Mineral

Broad Spectrum Sunscreen

SPF 30 PA+++

1.5 fl. oz./45 ml